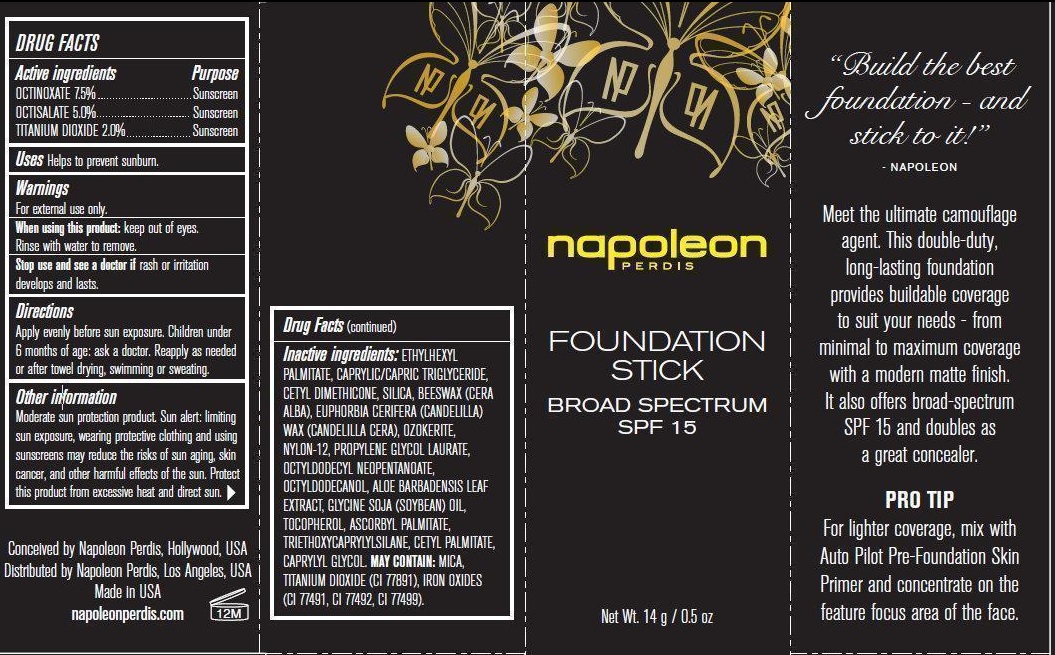 DRUG LABEL: Stick Foundation SPF SOFT BEIGE
NDC: 59735-444 | Form: CREAM
Manufacturer: MANA PRODUCTS, INC.
Category: otc | Type: HUMAN OTC DRUG LABEL
Date: 20240105

ACTIVE INGREDIENTS: OCTISALATE 5 g/100 g; TITANIUM DIOXIDE 2 g/100 g; OCTINOXATE 7.5 g/100 g
INACTIVE INGREDIENTS: SILICON DIOXIDE; NYLON-12; OCTYLDODECYL NEOPENTANOATE; ALOE VERA LEAF; ASCORBYL PALMITATE; TRIETHOXYCAPRYLYLSILANE; CETYL PALMITATE; OCTYLDODECANOL; MEDIUM-CHAIN TRIGLYCERIDES; YELLOW WAX; CANDELILLA WAX; PROPYLENE GLYCOL MONOLAURATE; CAPRYLYL GLYCOL; MICA; FERRIC OXIDE RED; FERRIC OXIDE YELLOW; FERROSOFERRIC OXIDE; ETHYLHEXYL PALMITATE; TOCOPHEROL; SOYBEAN OIL

STICK FOUNDATION BROAD SPECTRUM SPF 15 SOFT BEIGE

ACTIVE INGREDIENTS

OCTINOXATE 7.5%
OCTISALATE 5.0%
TITANIUM DIOXIDE 2.0%

PURPOSE

Sunscreen

USE

Helps to prevent sunburn.

WARNINGS

For external use only
Do not use on damaged or broken skin
When using this product keep out of eyes. Rinse with water to remove.
.

DIRECTIONS

Apply liberally 15 minutes before sun exposure
Reapply at least every 2 hours
Use water resistant sunscreen if swimming or sweathing
Sun Protection Measures: Spending time in the sun decreases risk of skin cancer and early again. To decrease this risk, regulaory use a sunscreen with a Broad Spectrum SPF value of 15 or higher and other sun protection measures including: Limit time in the sun especially from 10:00 am - 2:00 pm. Wear long sleeved shirts, pants, hats and sunglasses.
Children under 6 months: ask a doctor

INACTIVE INGREDIENTS

Alumina, Aluminum Hydroxide, Behenyl Alcohol, Butylene Glycol, C12-15 Alkyl Benzoate, Caprylic/Capric/Myristic/Stearic Triglyceride, Caprylyl Glycol, Carbomer, Cellulose Gum, Cety Alcohol, Dextrin Palmitate, Dimethicone, Dimethylacrylamide/Acrylic Acid/Plystyrene Ethyl Methacylate, Disodium EDTA, Ethoxydiglycol, Ethylhexylglycerin, Glycerin, Hexylene Glycol, Hydrogenated Lecithin, Isostearic Acid, Lycium Barbarum Fruit Extract, Lysine, Magnesium Chloride, Nordihydroguaiaretic Acid, Octyldodecyl Neopenanoate, Oleanolic Acid, Palmitoyl Hexapeptide-14, Panthenol, PEG-60 Almond Glycerides, Phenoxyethanol, Phospholipids, Phytantriol, Polygleceryl-3 Diisostearate, Polysorbate 80, Potassium Chloride, Silica, Sodium Benozate, Sodium Chloride, Sodium Dehydroacetate, Sodium Hyaluronate Crosspolymer, Sodium Hydroxide, Squalane, Steareth-2, Steareth-21, Stearic Acid, Superoxide Dismutase, Tetrahexyldecyl Ascorbate, Tocopherol, Tocopheryl Acetate, Triethoxycaprylylsilane, Triethylhexanoin, Water, Xanthan Gum, Zinc Chloride May Contain (+/-): Mica, Iron Oxides.

OTHER INFORMATION

Protect this product form excessive heat and direct sun

Stop use and ask a doctor if rash occurs.

RECENT MAJOR CHANGES

dosage & admin update

Keep out of reach of children. If product is swallowed, get medical help or contact a Poison Control Center right away.